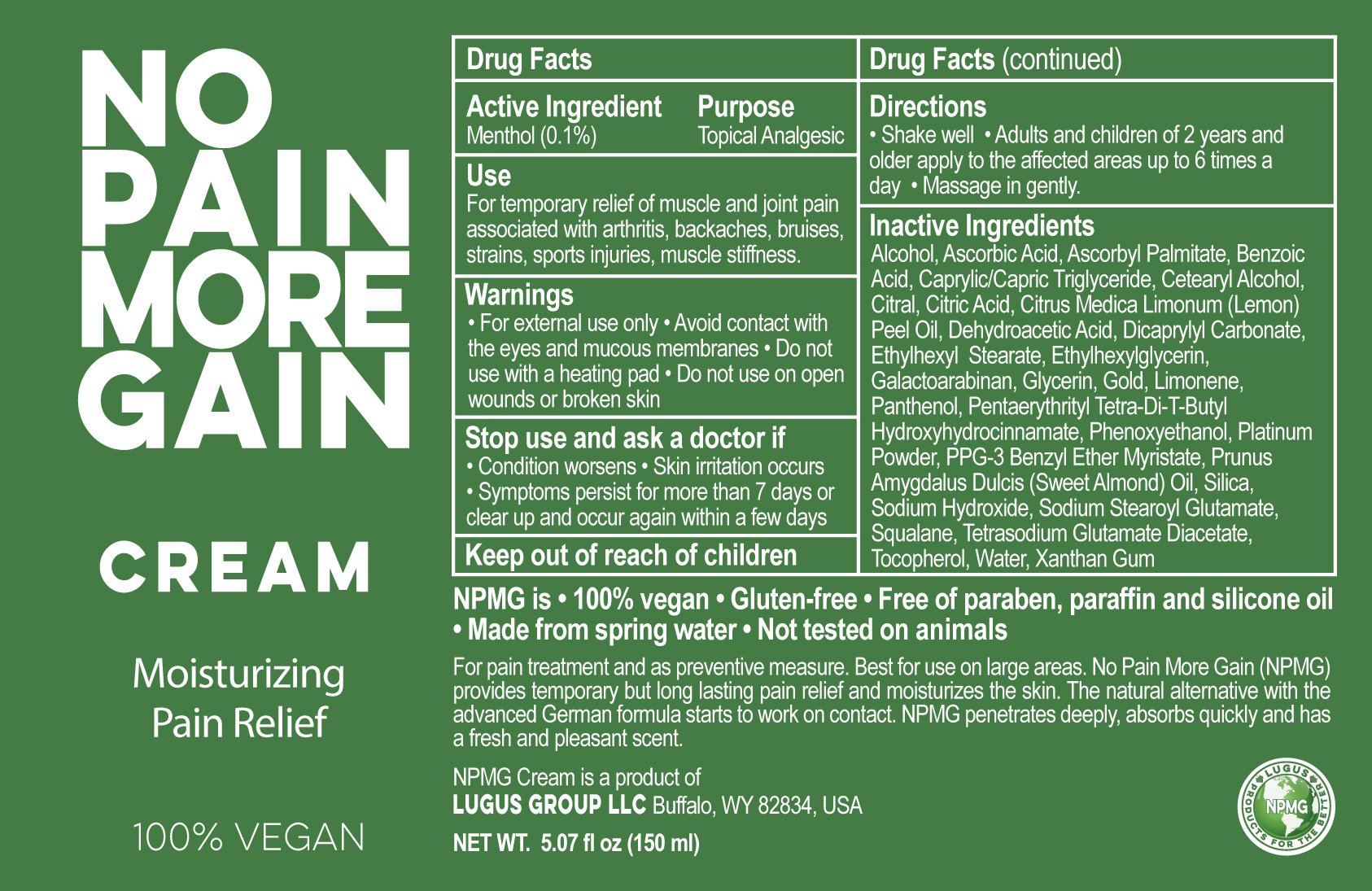 DRUG LABEL: No Pain More Gain
NDC: 69161-001 | Form: CREAM
Manufacturer: Lugus Group LLC
Category: otc | Type: HUMAN OTC DRUG LABEL
Date: 20191217

ACTIVE INGREDIENTS: MENTHOL 10 mg/100 mg
INACTIVE INGREDIENTS: PENTAERYTHRITOL TETRAKIS(3-(3,5-DI-TERT-BUTYL-4-HYDROXYPHENYL)PROPIONATE); GOLD; WATER; DICAPRYLYL CARBONATE; ETHYLHEXYL STEARATE; GLYCERIN; CETOSTEARYL ALCOHOL; ALMOND OIL; SODIUM STEAROYL GLUTAMATE; PPG-3 BENZYL ETHER MYRISTATE; PANTHENOL; SQUALANE; XANTHAN GUM; GALACTOARABINAN; LEMON OIL; PHENOXYETHANOL; BENZOIC ACID; LIMONENE, (+)-; SILICON DIOXIDE; TOCOPHEROL; TETRASODIUM GLUTAMATE DIACETATE; CAPRYLIC/CAPRIC/LAURIC TRIGLYCERIDE; ASCORBYL PALMITATE; ANHYDROUS CITRIC ACID; ASCORBIC ACID; SODIUM HYDROXIDE; PLATINUM; ETHYLHEXYLGLYCERIN; ALCOHOL; DEHYDROACETIC ACID; CITRAL

Active Ingredient

Menthol (0.1%)

Purpose

Topical Analgesic

Use

For temporary relief of muscle and joint pain associated with arthritis, backaches, bruises, strains, sports injuries and muscle stiffness

Keep out of reach of children.

Directions

Shake Well. Adults and children of 2 years and older apply to the affected areas up to 6 times a day. Massage in gently.

Warnings

• For external use only • Avoid contact with the eyes and mucous membranes • Do not use with a heating pad • Do not use on open wounds or broken skin

INDICATIONS AND USAGE

100% Vegan

No Pain More Gain Cream

Moisturizing Pain Relief

NPMG is • 100% vegan • Gluten-free • Free of paraben, paraffin and silicone oil • Made from spring water • Not tested on animals

For pain treatment and as preventive measure. Best for use on large areas. No Pain More Gain (NPMG) provides temporary but long lasting pain relief and moisturizes the skin. The natural alternative with the advanced German formula starts to work on contact. NPMG penetrates deeply, absorbs quickly and has a fresh and pleasant scent.

NPMG Cream is a product

Lugus Group LLC, Buffalo, WY 82834

NET WT 5.07 fl oz (150 ml)

Inactive Ingredients

Alcohol, Ascorbic Acid, Ascorbyl Palmitate, Benzoic Acid, Caprylic/Capric Triglyceride, Cetearyl Alcohol, Citral, Citric Acid, Citrus Medica Limonum (Lemon) Peel Oil, Dehydroacetic Acid, Dicaprylyl Carbonate, Ethylhexylglycerin, Ethylhexyl Stearate, Galactoarabinan, Glycerin, Gold, Limonene, Panthenol, Pentaerythrityl Tetra-Di-T-Butyl Hydroxyhydrocinnamate, Phenoxyethanol, Platinum Powder, PPG-3 Benzyl Ether Myristate, Prunus Amygdalus Dulcis (Sweet Almond) Oil, Silica, Sodium Hydroxide, Sodium Stearoyl Glutamate, Squalene, Tetrasodium Glutamate Diacetate, Tocopherol, Water, Xanthan gum.

Stop use and ask a doctor if

• Condition worsens • Skin irritation occurs • Symptoms persist for more than 7 days or clear up and occur again within a few days